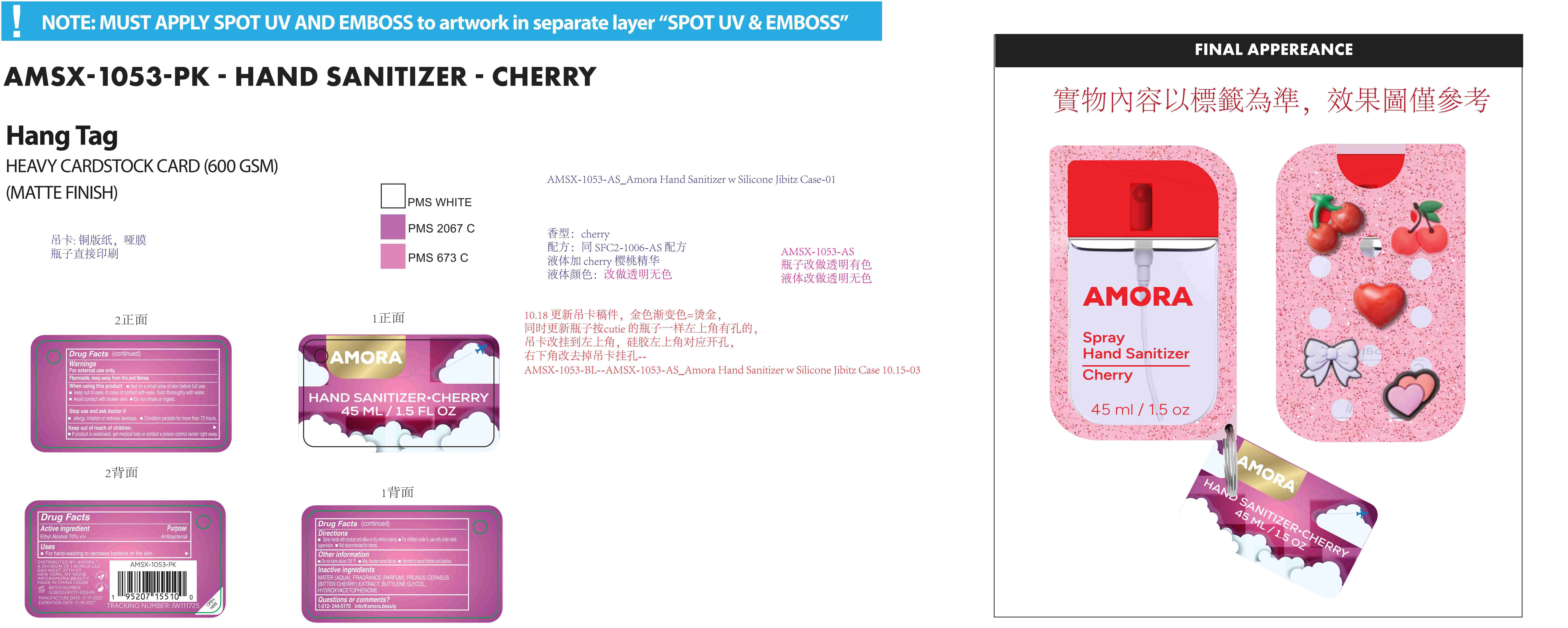 DRUG LABEL: AMORA Spray. Hand Sanitizer Cherry
NDC: 85161-139 | Form: SPRAY
Manufacturer: Longway Technology(Guangzhou) Co., Ltd.
Category: otc | Type: HUMAN OTC DRUG LABEL
Date: 20251201

ACTIVE INGREDIENTS: ALCOHOL 0.7 mL/1 mL
INACTIVE INGREDIENTS: PRUNUS CERASUS (BITTER CHERRY) FLOWER EXTRACT; WATER; FRAGRANCE 13576; BUTYLENE GLYCOL; HYDROXYACETOPHENONE

ACTIVE INGREDIENT

Ethyl Alcohol 70% v/v--------Antibacterial

KEEP OUT OF REACH OF CHILDREN

If product is swallowed, get medical help or contact a poison control center right away.

Inactive ingredients:

WATER (AQUA), FRAGRANCE (PARFUM), PRUNUS CERASUS(BITTER CHERRY) EXTRACT, BUTYLENE GLYCOL, HYDROXYACETOPHENONE.

Uses

For hand-washing to decrease bacteria on the skin.

Directions

Spray hands with product and allow to dry without wiping.

For children under 6, use only under adult supervision.

Not recommended for infants.

Other information

Do not store above 105°F
May discolor some fabrics

Harmful to wood finishes and plastics

QUESTIONS

1-212-244-5170 info@amora.beauty

PURPOSE

Antibacterial

Warnings
For external use only.
Flammable, keep away from fire and flames

When using this product

test on a small area of skin before full use.
keep out of eyes. In case of contact with eyes, flush thoroughly with water.
Avoid contact with broken skin.

Do not inhale or ingest.

Stop use and ask doctor if

allergy, irritation or redness develops. C

ondition persists for more than 72 hours.

Keep out of reach of children.
lf product is swallowed, get medical help or contact a poison control center right away.